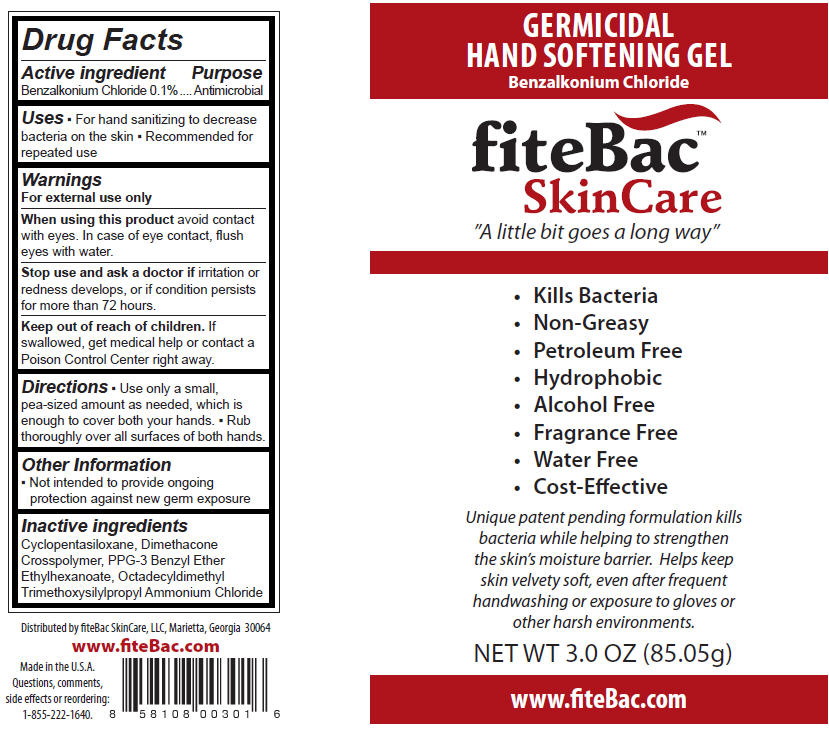 DRUG LABEL: fiteBac SkinCare 
NDC: 13136-001 | Form: GEL
Manufacturer: fiteBac SkinCare, LLC
Category: otc | Type: HUMAN OTC DRUG LABEL
Date: 20111110

ACTIVE INGREDIENTS: Benzalkonium Chloride 0.029 mL/29.57 mL
INACTIVE INGREDIENTS: Cyclomethicone 5

Germicidal
Hand Softening Gel
Benzalkonium Chloride

Drug Facts

Active ingredient

Benzalkonium Chloride 0.1%

Purpose

Antimicrobial

Uses

- For hand sanitizing to decrease bacteria on the skin
- Recommended for repeated use

Warnings

For external use only

When using this product avoid contact with eyes. In case of eye contact, flush eyes with water.

Stop use and ask a doctor if irritation or redness develops, or if condition persists for more than 72 hours.

Keep out of reach of children. If swallowed, get medical help or contact a Poison Control Center right away.

Directions

- Use only a small, pea-sized amount as needed, which is enough to cover both your hands.
- Rub thoroughly over all surfaces of both hands

Other Information

- Not intended to provide ongoing protection against new germ exposure

Inactive ingredients

Cyclopentasiloxane, Dimethacone Crosspolymer, PPG-3 Benzyl Ether Ethylhexanoate, Octadecyldimethyl Trimethoxysilylpropyl Ammonium Chloride

Questions, comments, side effects or reordering

1-855-222-1640.

Distributed by fiteBac SkinCare, LLC, Marietta, Georgia 30064

PRINCIPAL DISPLAY PANEL - 85.05 g Tube Label

GERMICIDAL
HAND SOFTENING GEL
Benzalkonium Chloride

fiteBac™
SkinCare
"A little bit goes a long way"

- Kills Bacteria
- Non-Greasy
- Petroleum Free
- Hydrophobic
- Alcohol Free
- Fragrance Free
- Water Free
- Cost-Effective

Unique patent pending formulation kills
bacteria while helping to strengthen
the skin's moisture barrier. Helps keep
skin velvety soft, even after frequent
handwashing or exposure to gloves or
other harsh environments.

NET WT 3.0 OZ (85.05g)

www.fiteBac.com